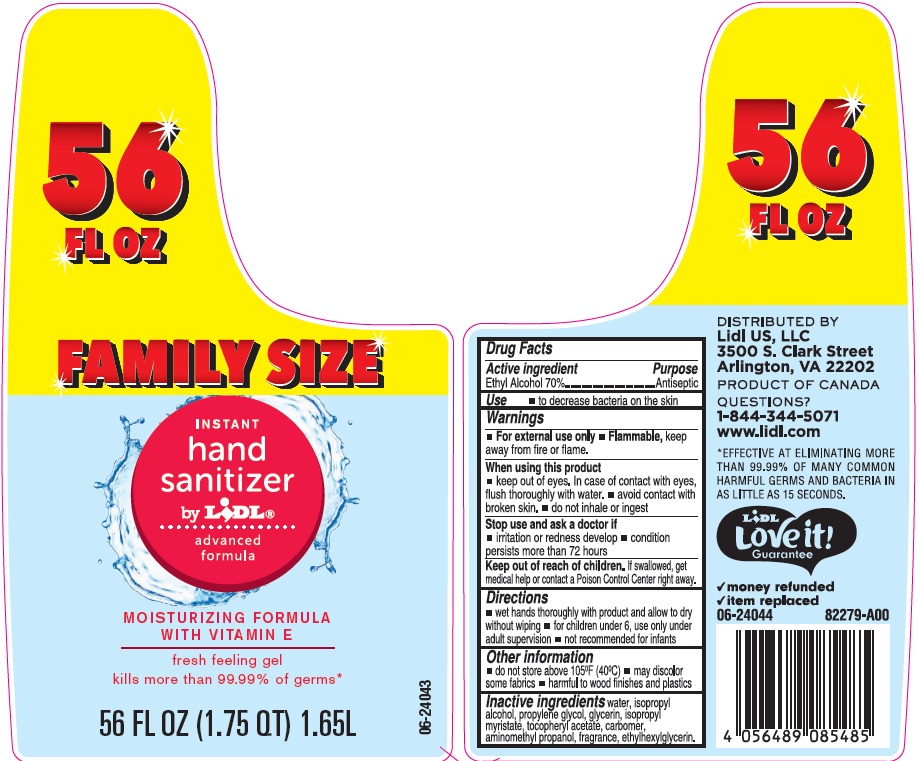 DRUG LABEL: Lidl Instant Hand Sanitizer
NDC: 63148-017 | Form: LIQUID
Manufacturer: Apollo Health and Beauty Care Inc.
Category: otc | Type: HUMAN OTC DRUG LABEL
Date: 20190903

ACTIVE INGREDIENTS: ALCOHOL 700 mg/1 mL
INACTIVE INGREDIENTS: WATER; ISOPROPYL ALCOHOL; PROPYLENE GLYCOL; GLYCERIN; ISOPROPYL MYRISTATE; .ALPHA.-TOCOPHEROL ACETATE, DL-; CARBOMER 934; AMINOMETHYLPROPANOL; ETHYLHEXYLGLYCERIN

Drug Facts

Active ingredient

Ethyl Alcohol 70%

Purpose

Antiseptic

Uses

- to decrease bacteria on the skin

Warnings

For external use only

- flammable, keep away from fire or flame

When using this product

- keep out of eyes. In case of conact with eyes, flush thoroughly with water.
- avoid contact with broken skin.
- do not inhale or ingest.

Stop use and ask a doctor if

- irritation or redness develop
- condition persists more than 72 hours

Keep out of reach of children.

If swallowed, get medical help or contact a Poison Control Center right away.

Directions

- wet hands thoroughly with product and allow to dry without wiping
- for children under 6, use only under adult supervision
- not recommended for infants

Other information

- do not store above 105°F (40°C)
- may discolor some fabrics
- harmful to wood finishes and plastics

Inactive ingredients

Water (Aqua), Isopropyl Alcohol, Propylene Glycol, Glycerin, Isopropyl Myristate, Tocopheryl Acetate, Carbomer, Aminomethyl Propanol, Fragrance (Parfum), Ethylhexylglycerin.